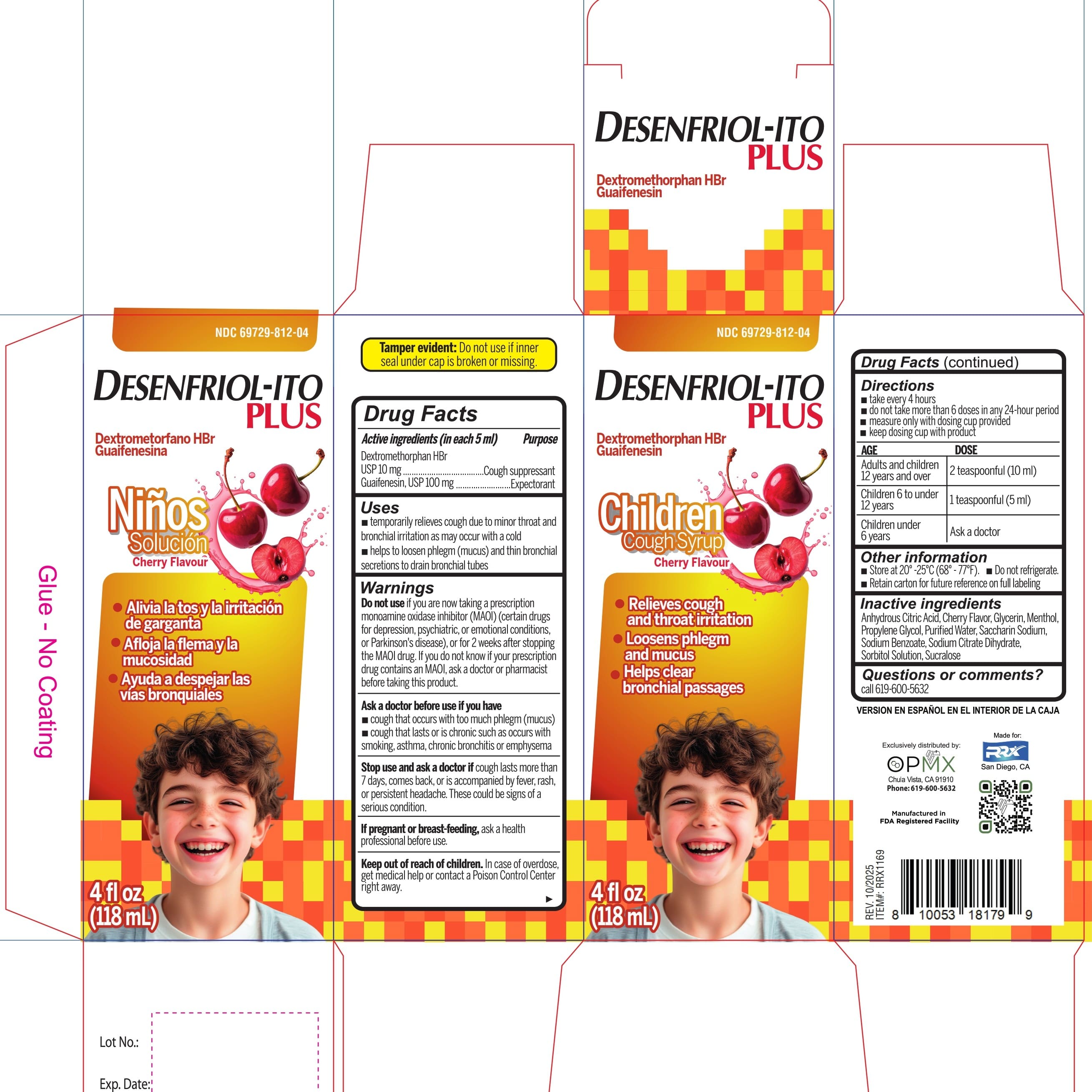 DRUG LABEL: DEXTROMETHORPHAN HYDROBROMIDE and GUAIFENESIN
NDC: 69729-812 | Form: SYRUP
Manufacturer: OPMX LLC
Category: otc | Type: HUMAN OTC DRUG LABEL
Date: 20251015

ACTIVE INGREDIENTS: DEXTROMETHORPHAN HYDROBROMIDE 10 mg/5 mL; GUAIFENESIN 100 mg/5 mL
INACTIVE INGREDIENTS: SODIUM CITRATE, UNSPECIFIED FORM; SUCRALOSE; ANHYDROUS CITRIC ACID; GLYCERIN; MENTHOL; PROPYLENE GLYCOL; WATER; SODIUM BENZOATE; SACCHARIN SODIUM; SORBITOL

Desenfriol-ito PLUS

Active Ingredient (in each 5 mL) Purpose

Dextromethorphan HBr USP 10 mg............. Cough suppressant

Guaifenesin, USP 100 mg............................... Expectorant

PURPOSE

- Cough suppressant
- Expectorant

Uses

- temporarily relieves cough due to minor throat and bronchial irritation as may occur with a cold
- helps to loosen phlegm (mucus) and thin bronchial secretions to drain bronchial tubes

Warnings

Do not use

- Do not useif you are now taking a prescription monoamine oxidase inhibitor (MAOI) (certain drugs for depression, psychiatric, or emotional conditions, or Parkinson's disease), or for 2 weeks after stopping the MAOI drug. If you do not know if your prescription drug contains an MAOI, ask a doctor or pharmacist before taking this product.

Ask a doctor before use if you have

- cough that occurs with too much phlegm (mucus)
- cough that lasts or is chronic such as occurs with smoking, asthma, chronic bronchitis or emphysema

Stop use and ask a doctor if

Stop use and ask a doctor ifcough lasts more than 7 days, comes back, or is accompanied by fever, rash, or persistent headache. These could be signs of a serious condition.

If pregnant or breast-feeding

ask a health professional before use

Keep out of reach of children. In case of overdose, get medical help or contact a Poison Control Center right away.

Directions

- take evey 4 hours
- do not take more than 6 doses in any 24-hour period
- measure only with dosing cup provided
- keep dosing cup with product

Age | Dose
Adults and children 12 years and over | 2 teaspoonful (10 mL)
Children 6 to under 12 years | 1 teaspoonful (5 mL)
Children under 6 years | Ask a doctor

Other information

- Store at 20°-25°C (68° -77°F).
- Do not refrigerate.
- Retain carton for future reference on full labeling

Inactive ingredients

anhydrous citric acid, cherry flavor, glycerin, menthol, propylene glycol, purified water, saccharin sodium, sodium benzoate, sodium citrate dihydrate, sorbitol solution, sucralose.

Questions or comments?
Call 619-600-5632

Tamper evident: Do not use if inner seal under cap is broken or missing.

Exclusively distributed by
OPMX
Chula Vista, CA91910
Phone: 619-600-5632

Manufactured in
FDA Registered Facility
In the USA